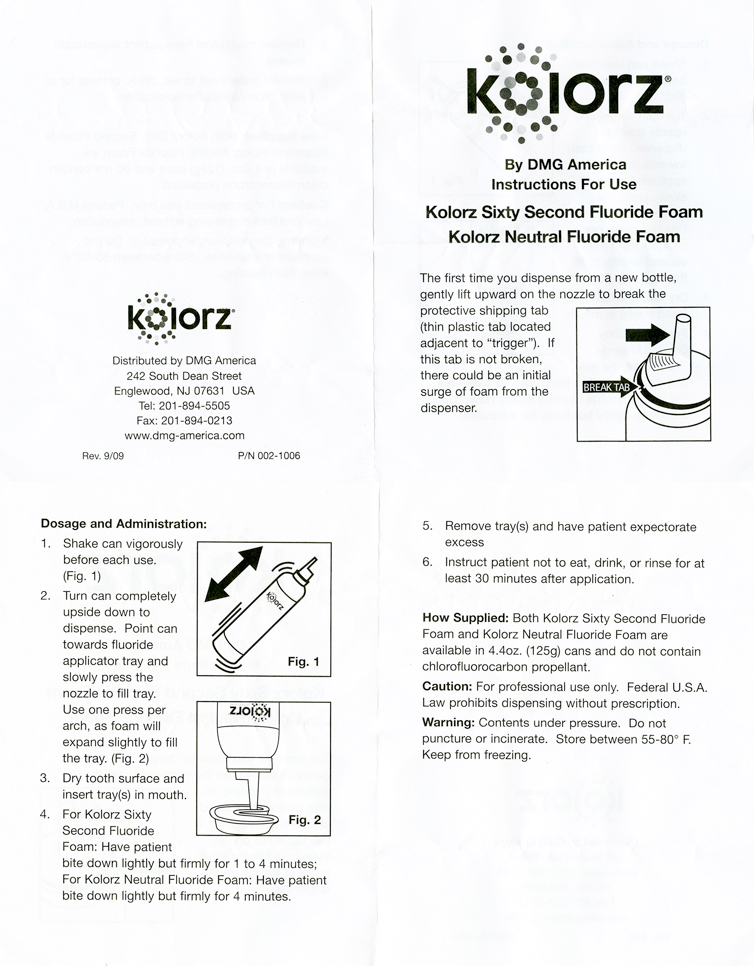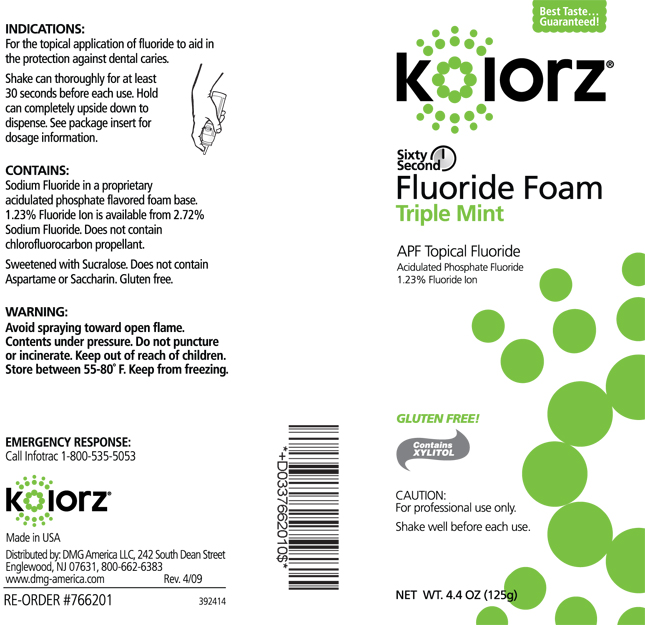 DRUG LABEL: kolorz
NDC: 10733-357 | Form: AEROSOL, FOAM
Manufacturer: Medical Products Laboratories, Inc.
Category: prescription | Type: HUMAN PRESCRIPTION DRUG LABEL
Date: 20110311

ACTIVE INGREDIENTS: SODIUM FLUORIDE 27.2 mg/1 g
INACTIVE INGREDIENTS: WATER; SUCRALOSE; XYLITOL; SODIUM PHOSPHATE, MONOBASIC; BETAINE; POLOXAMER 407

kolorz Sixty Second Fluoride Foam Triple Mint

Dosage and Administration
Shake can vigorously before each use. Turn can completely upside down to dispense. Point can towards fluoride applicator tray and slowly press the nozzle to fill tray. Use one press per arch, as foam will expand slightly to fill the tray. Dry tooth surface and insert tray(s) in mouth. Have patient bite down lightly but firmly for 1 to 4 minutes. Remove tray(s) and have patient expectorate excess. Instruct patient not to eat, drink, or rinse for at least 30 minutes after application.

DOSAGE AND ADMINISTRATION

Instructions For Use
The first time you dispense from a new bottle, gently lift upward on the nozzle to break the protective shipping tab (thin plastic tab located adjacent to "trigger"). If this tab is not broken, there could be an initial surge of foam from the dispenser.

DOSAGE AND ADMINISTRATION

CONTAINS
Sodium Fluoride in a proprietary acidulated phosphate flavored foam base. 1.23% Fluoride Ion is available from 2.72% Sodium Fluoride. Does not contain chlorofluorocarbon propellant. Sweetened with Sucralose. Does not contain Aspartame or Saccharin. Gluten free.

WARNINGS

WARNING Avoid spraying toward open flame. Contents under pressure. Do not puncture or incinerate. Keep out of reach of children. Store between 55-80 F. Keep from freezing.

PRECAUTIONS

CAUTION
For professional use only. Federal U.S.A. Law prohibits dispensing without prescription. Shake well before each use.

How Supplied
Kolorz Sixty Second Fluoride Foam is available in 4.4 oz. (125g) can and do not contain chlorofluorocarbon propellant.

INDICATIONS
For the topical application of fluoride to aid in the protection against dental caries. Shake can thoroughly for at least 30 seconds before each use. Hold can completely upside down to dispense. See package insert for dosage information.

PACKAGE LABEL

kolorz Sixty Second Fluoride Foam Triple Mint